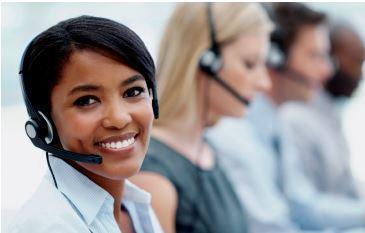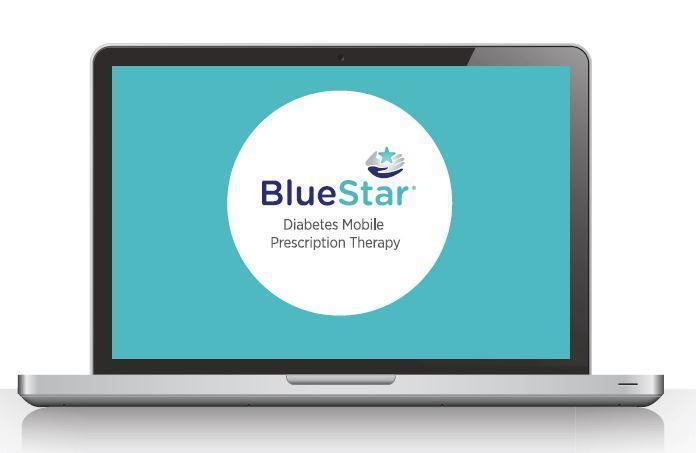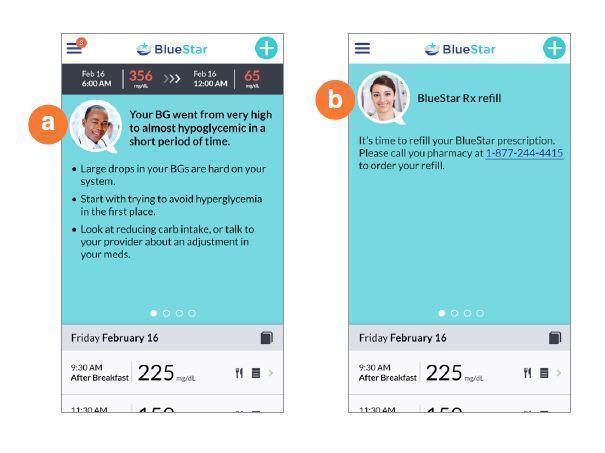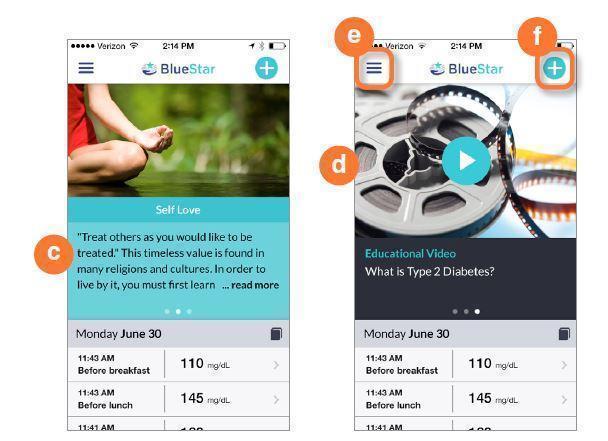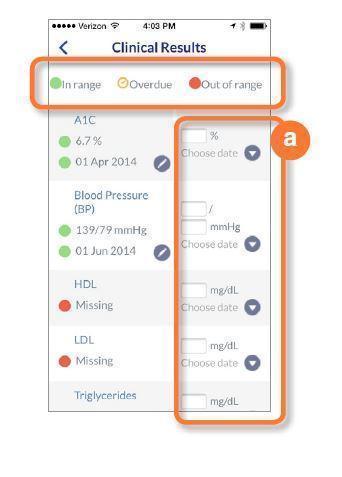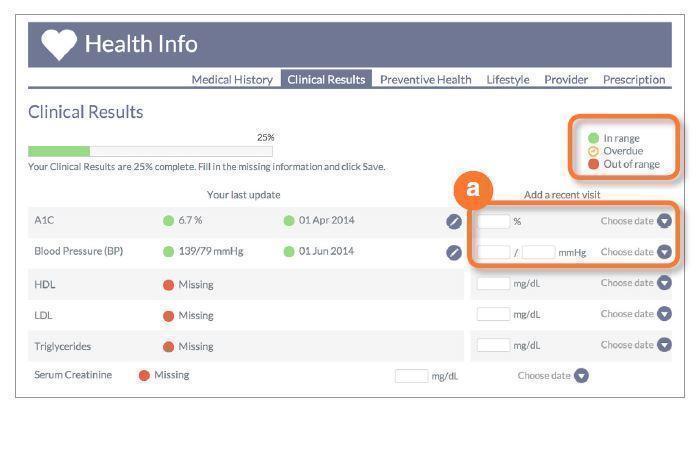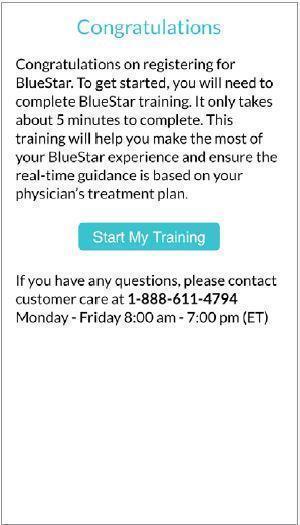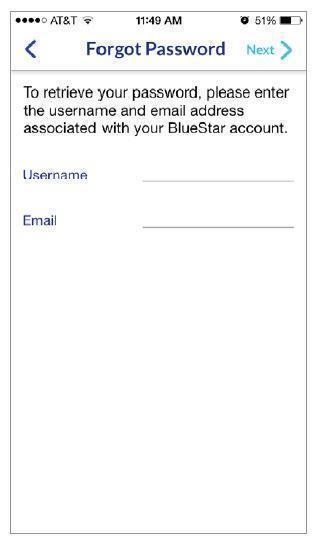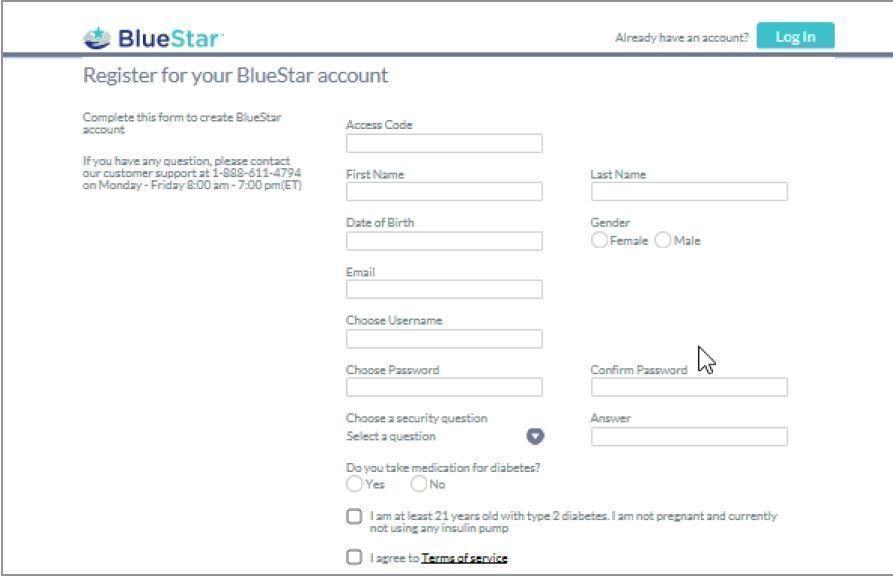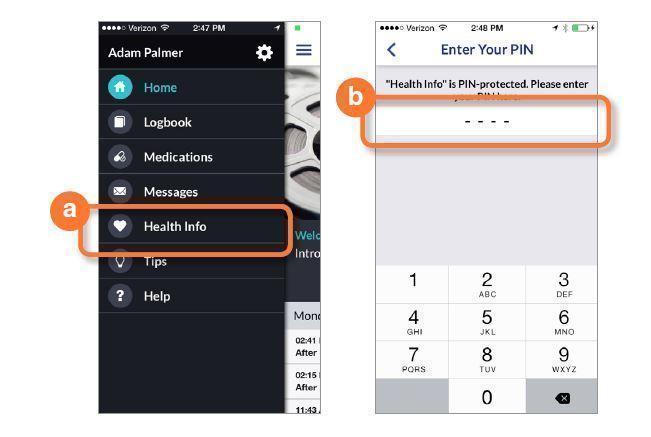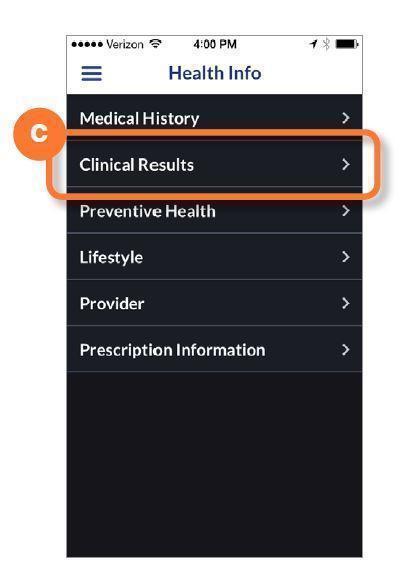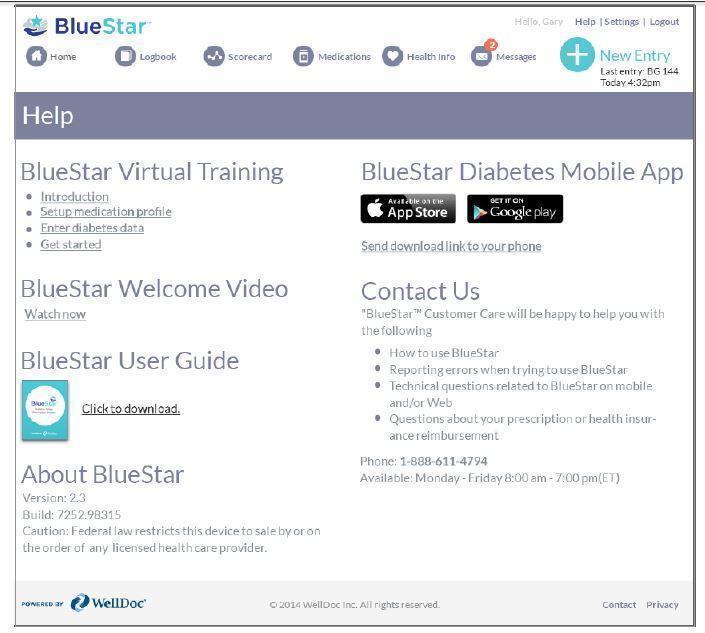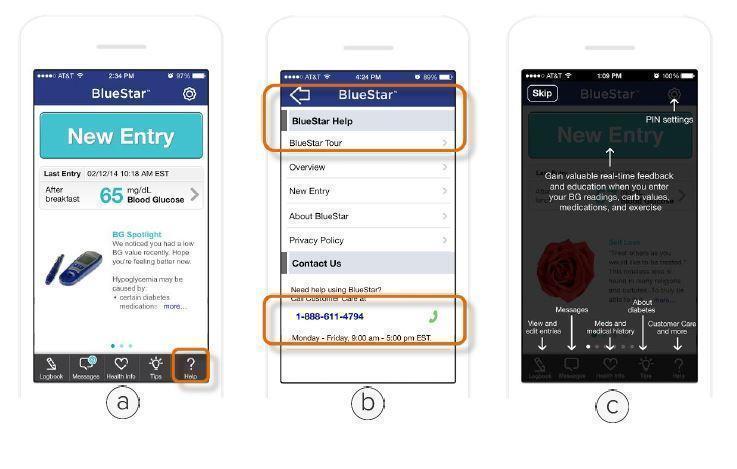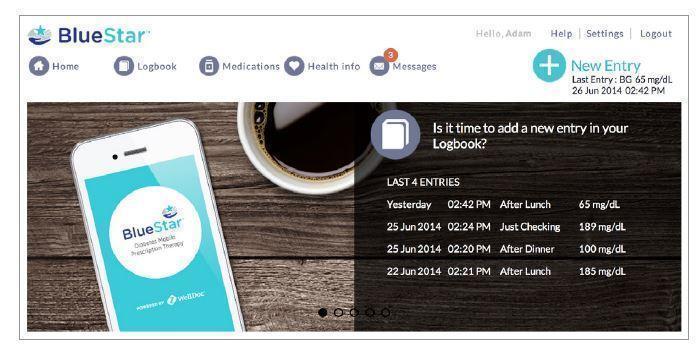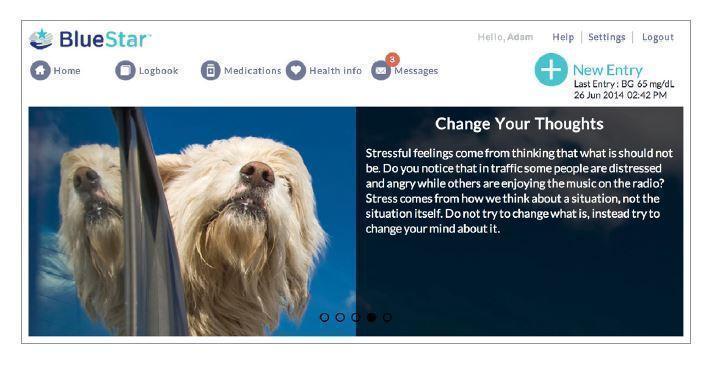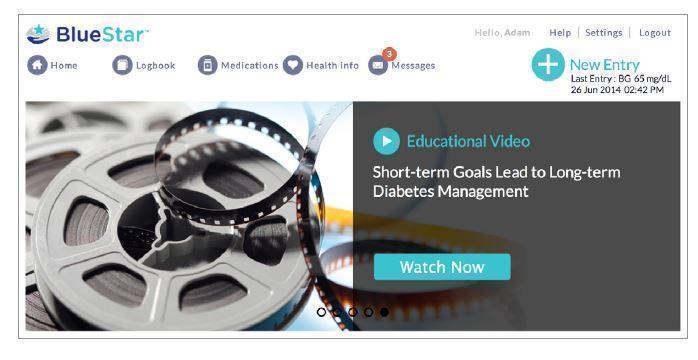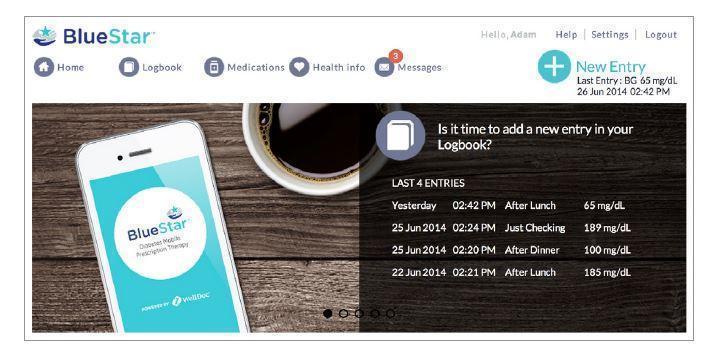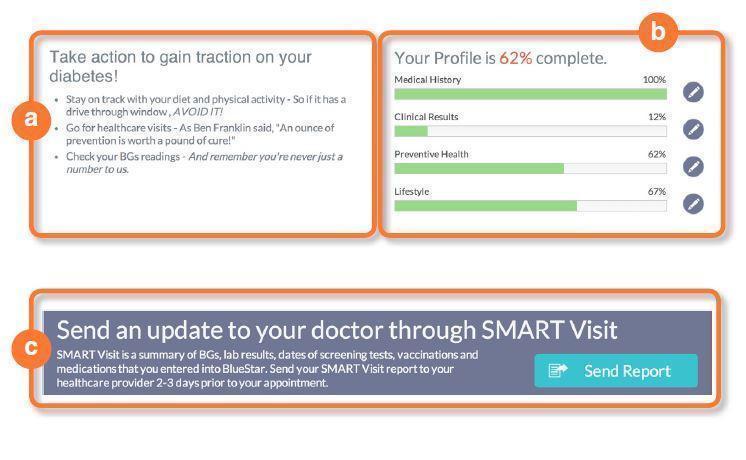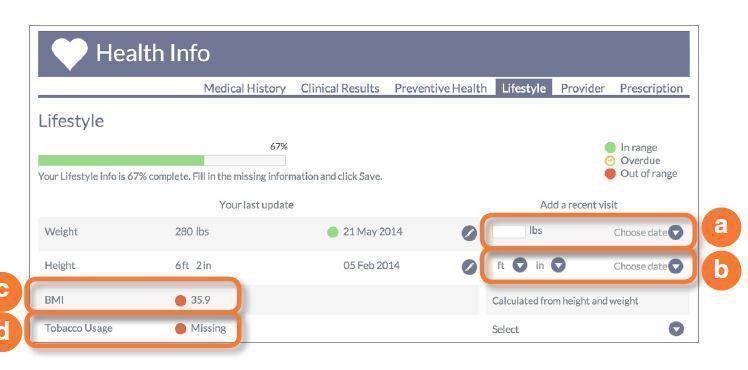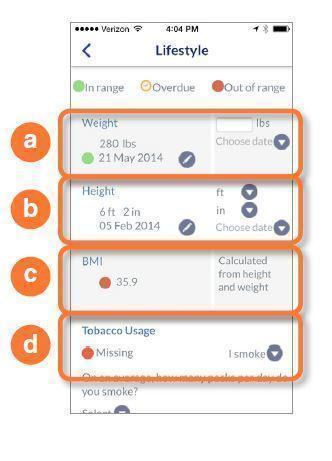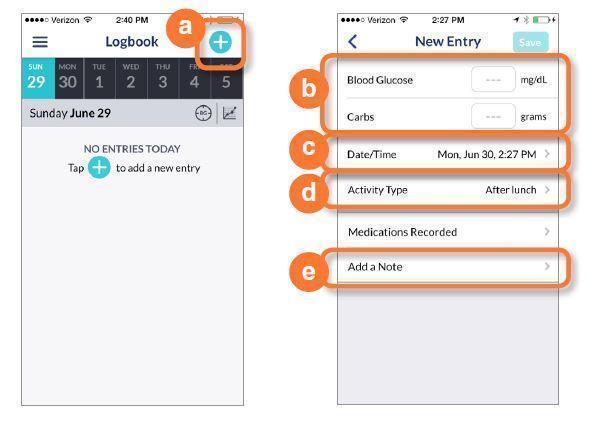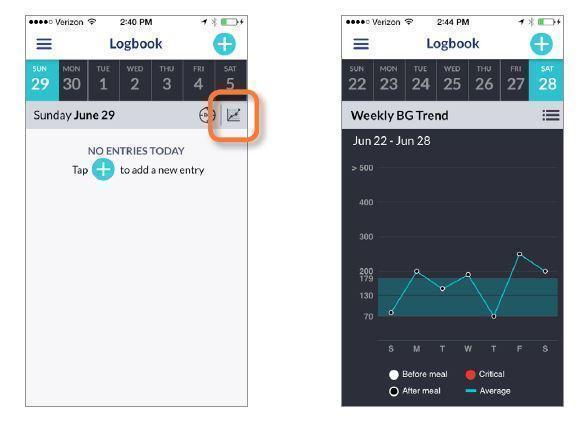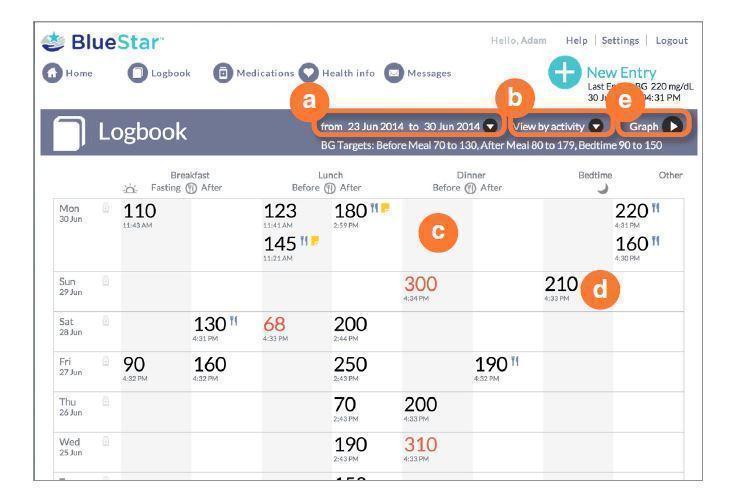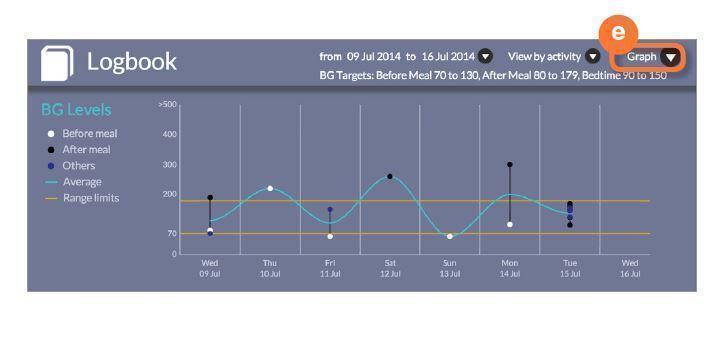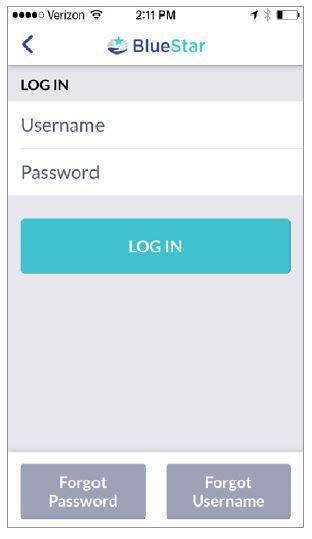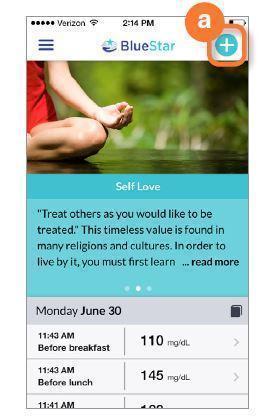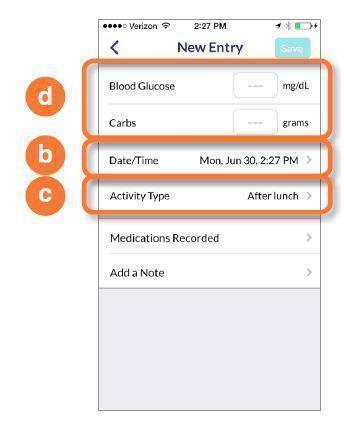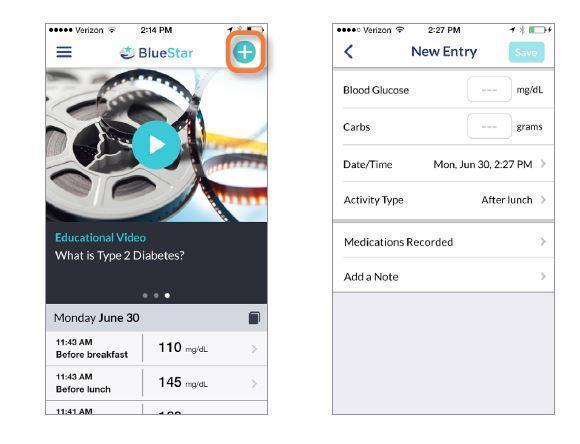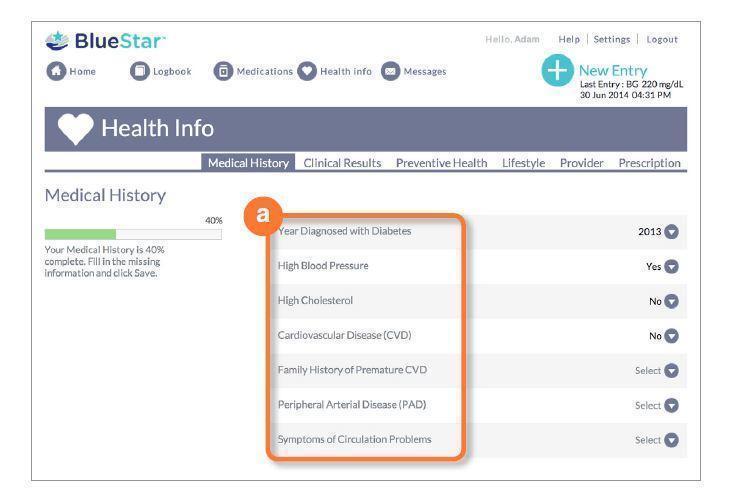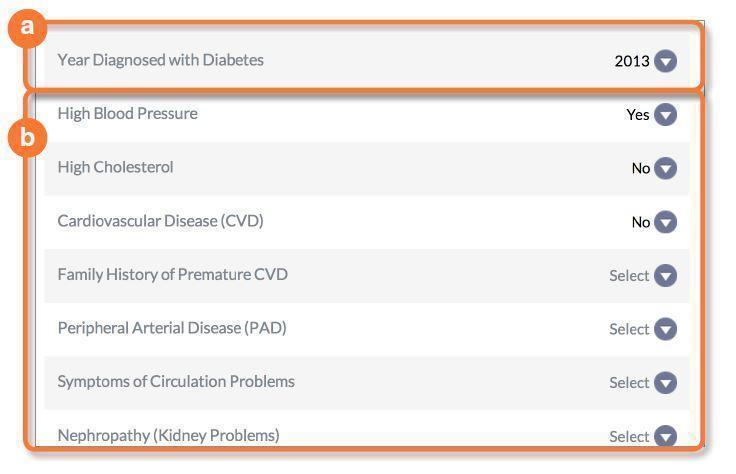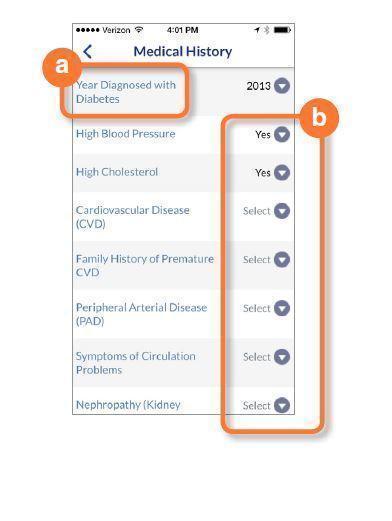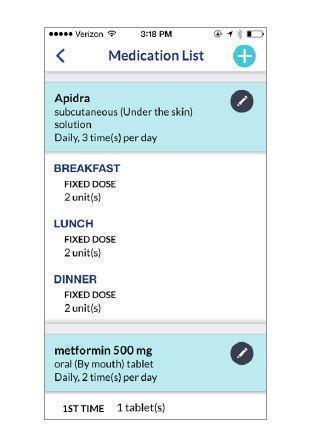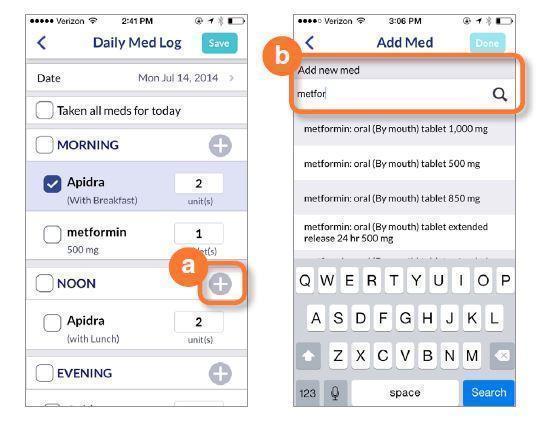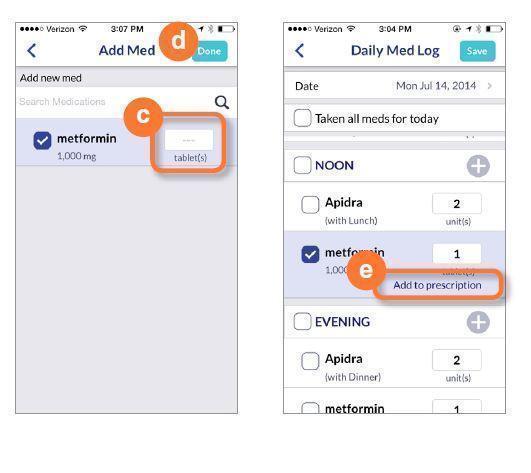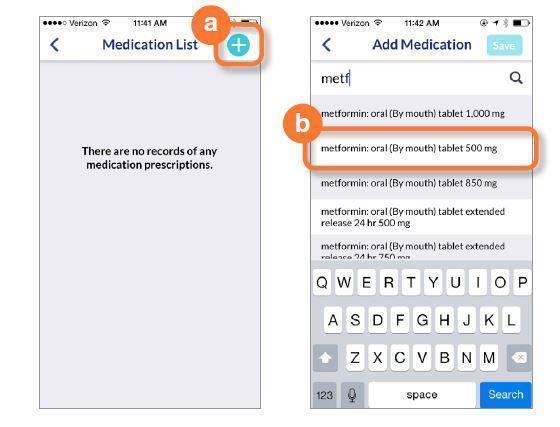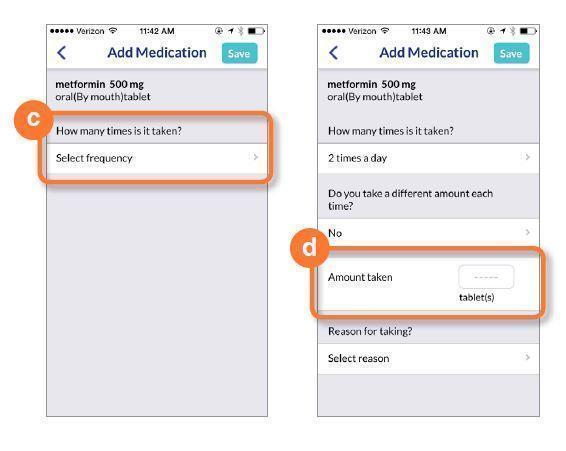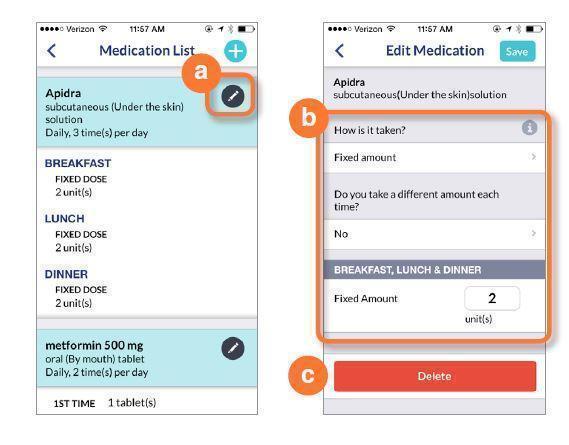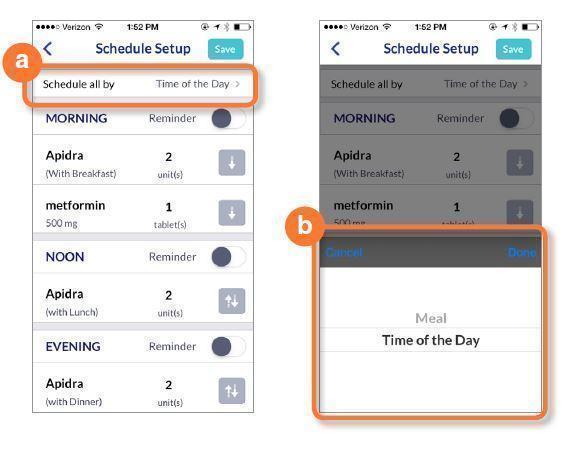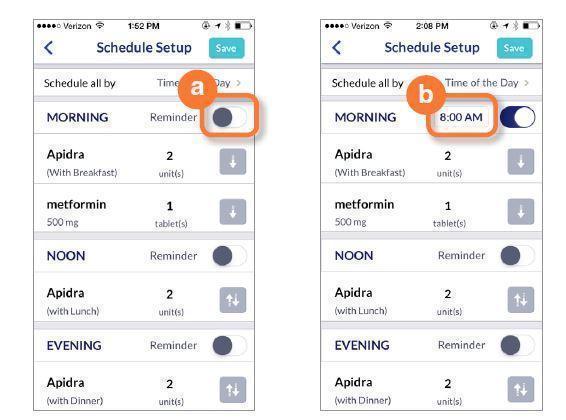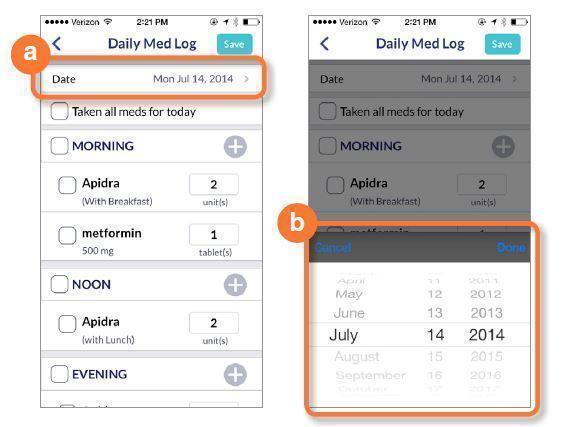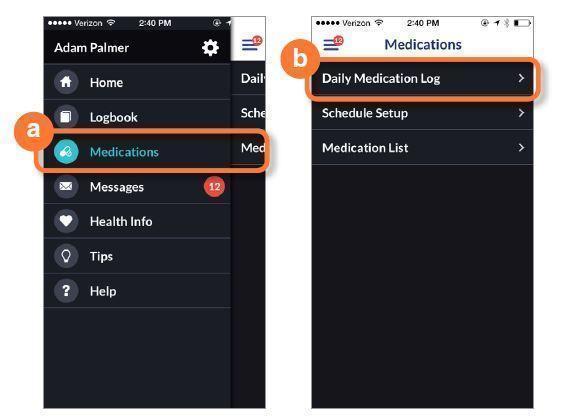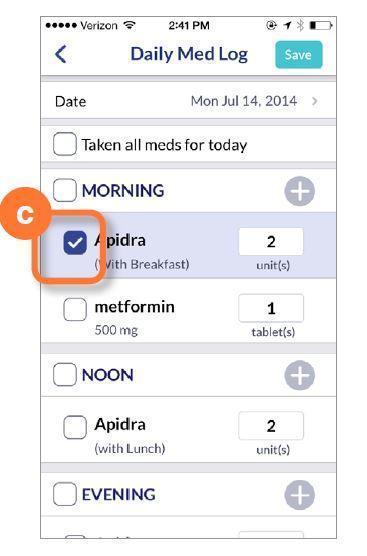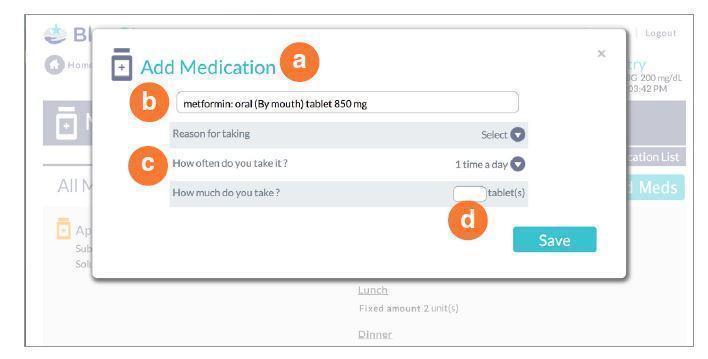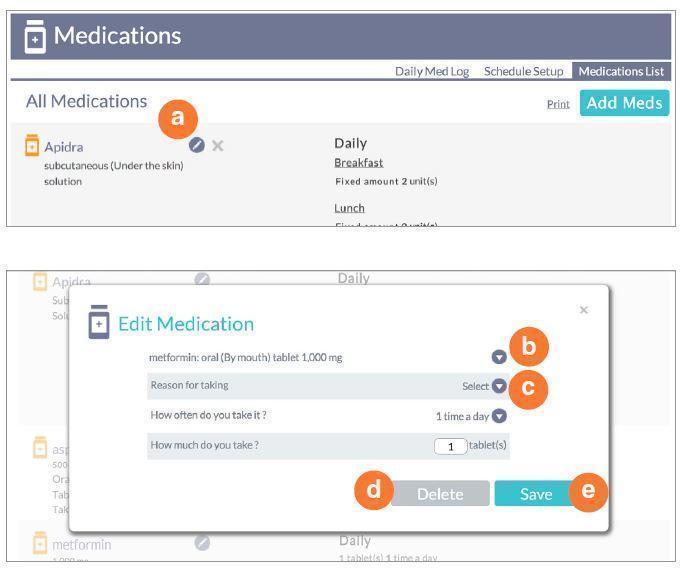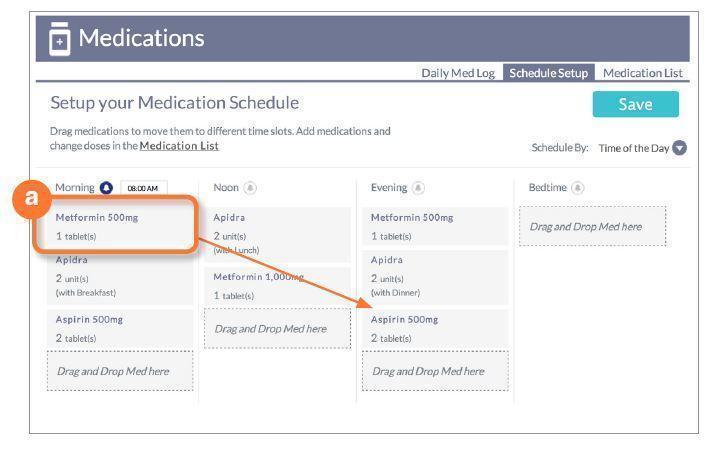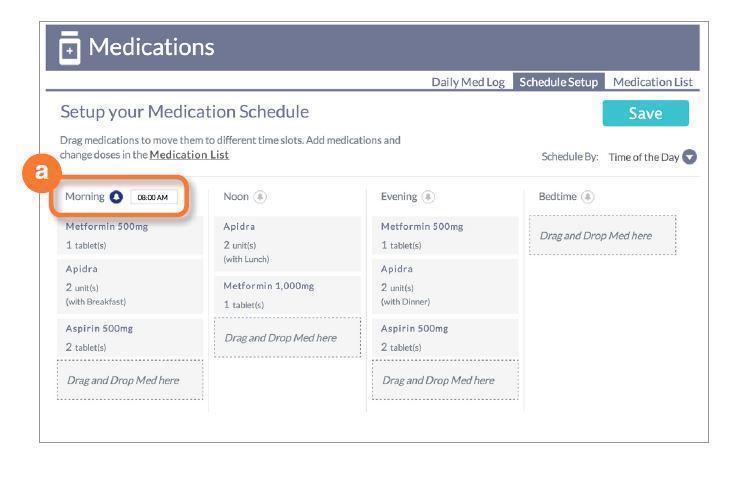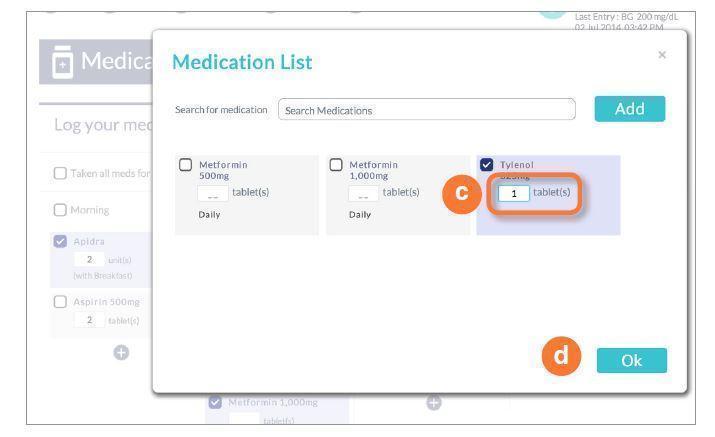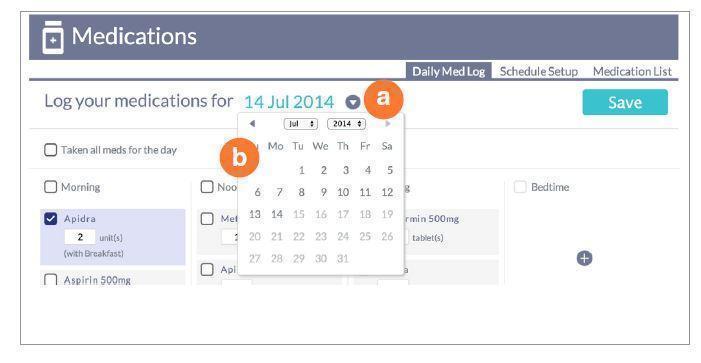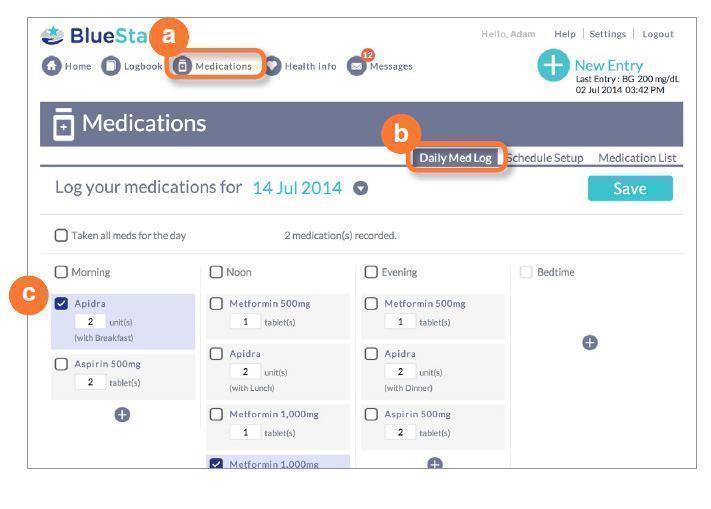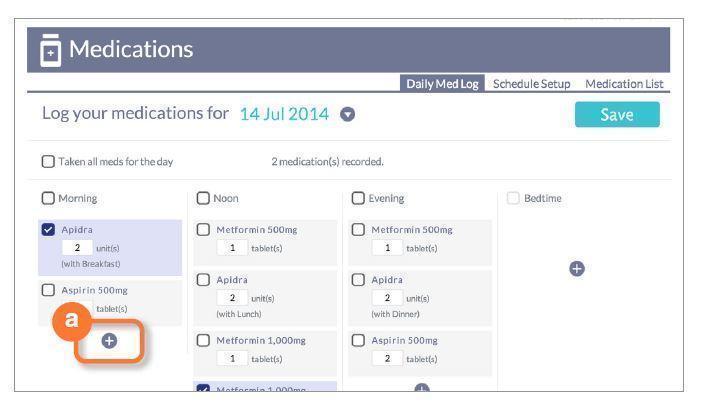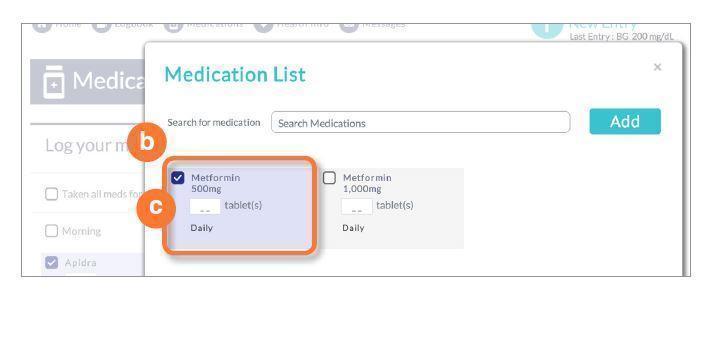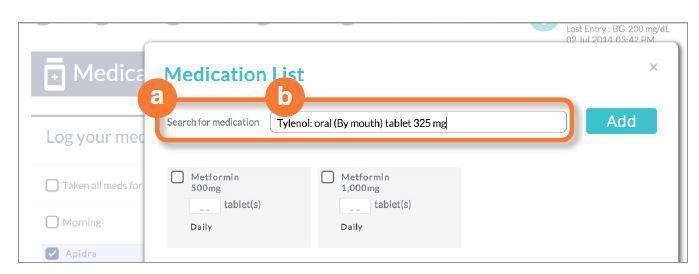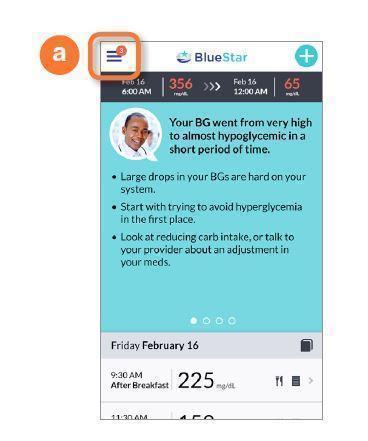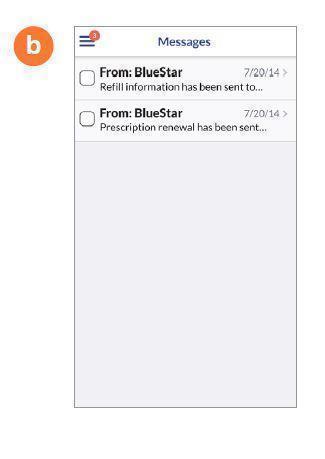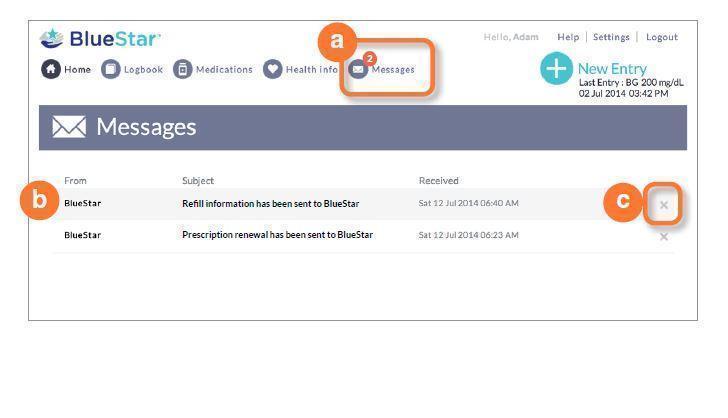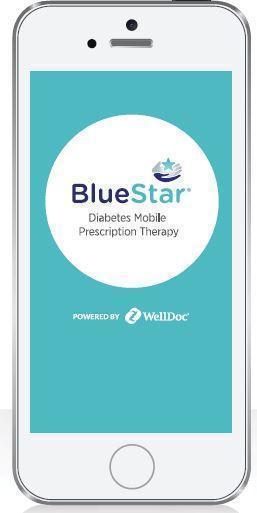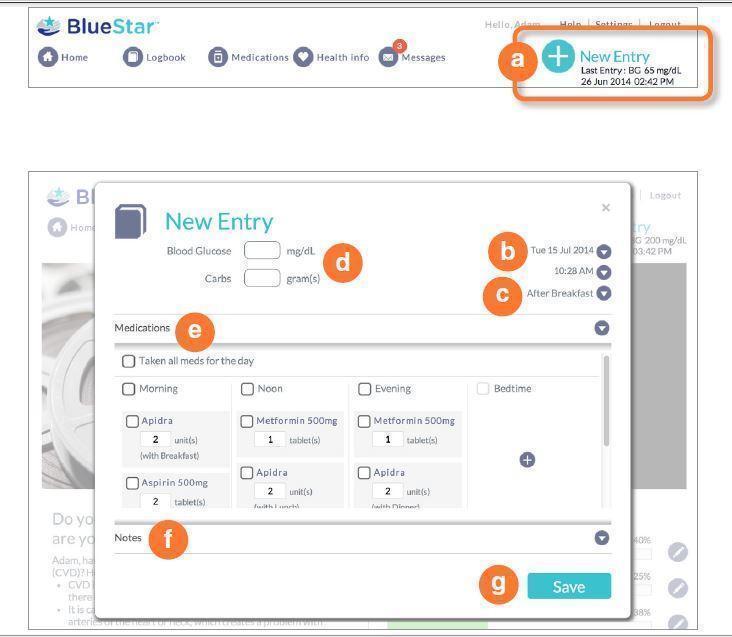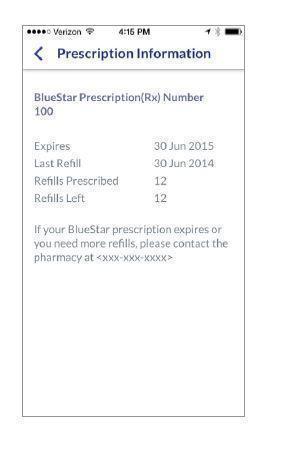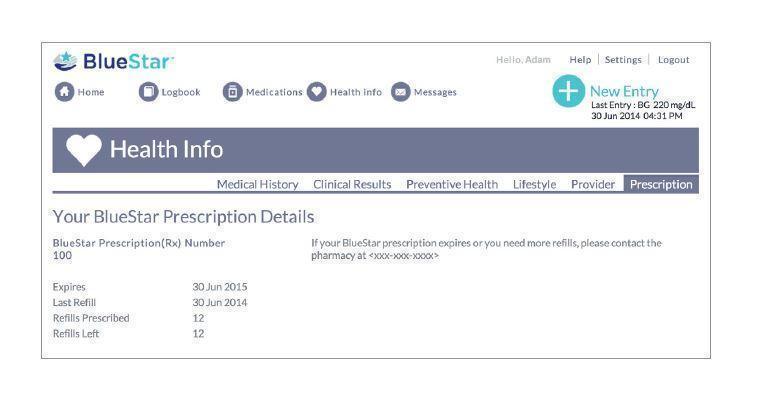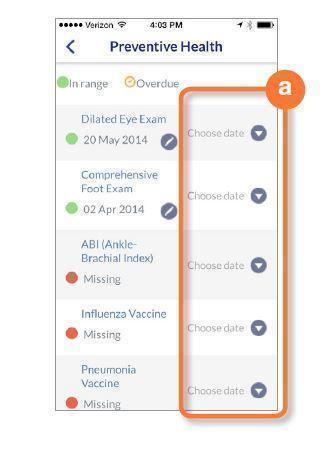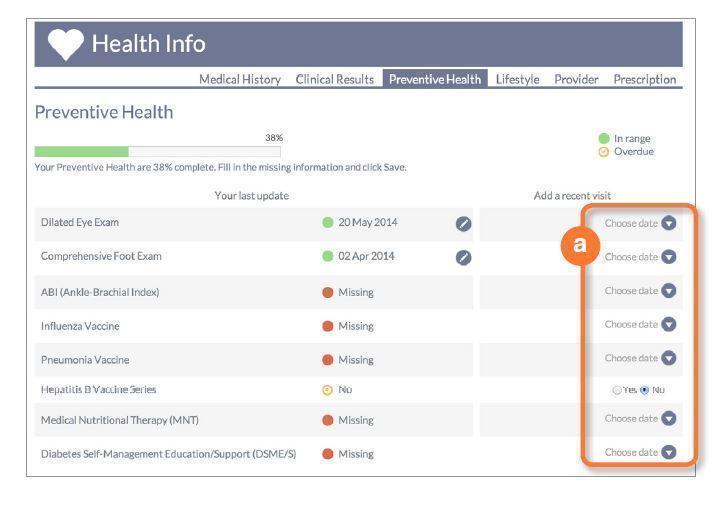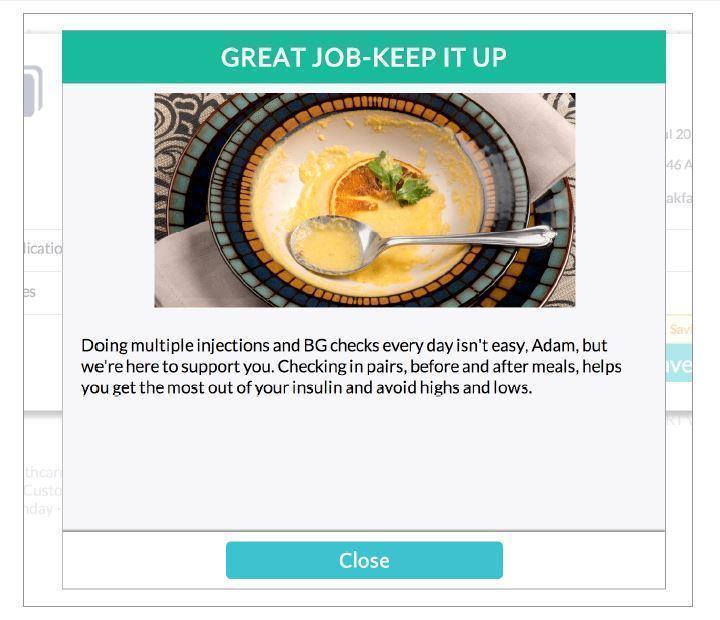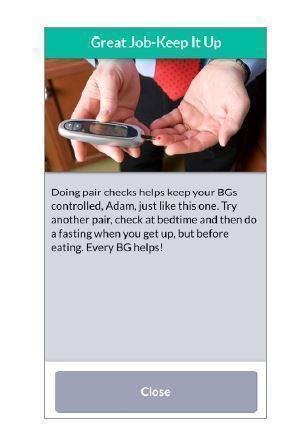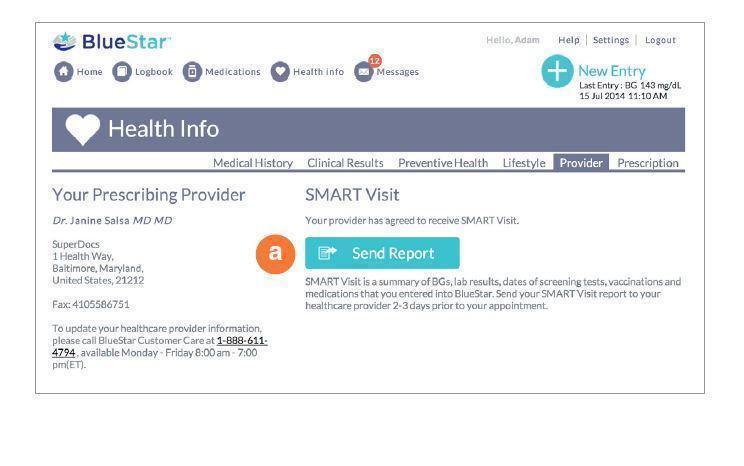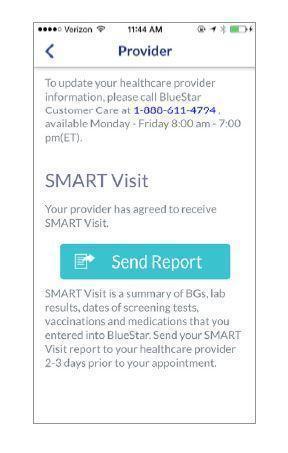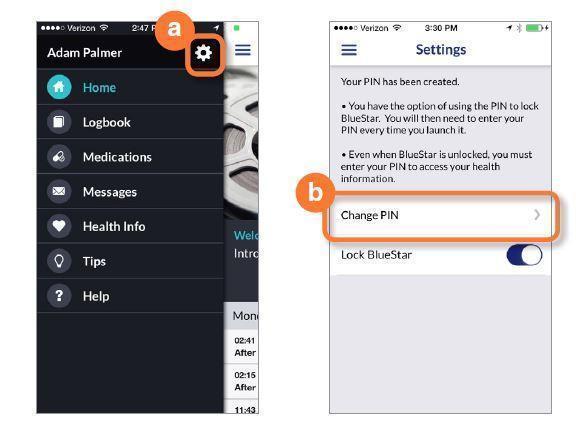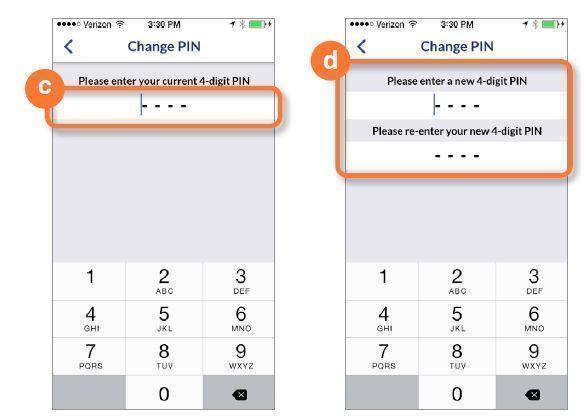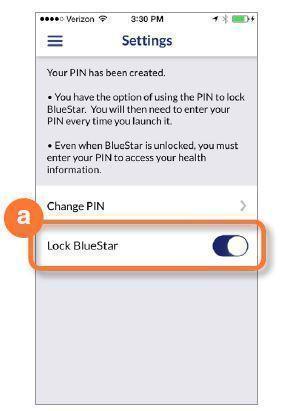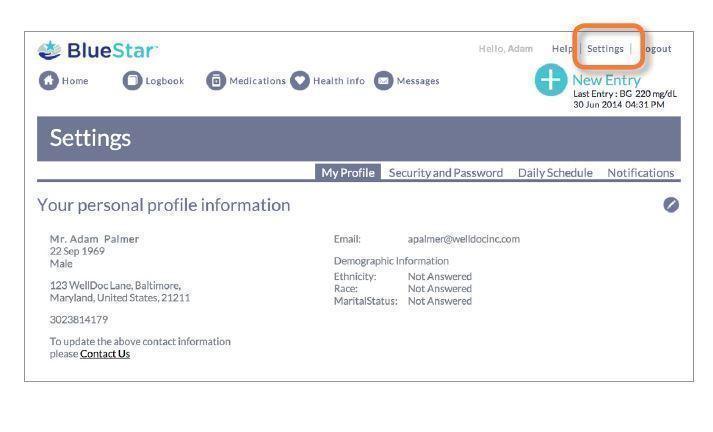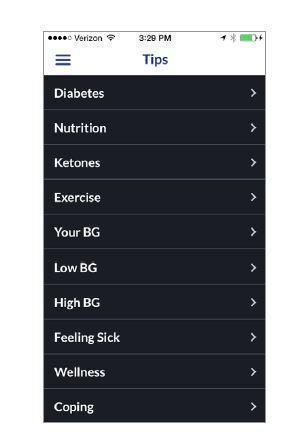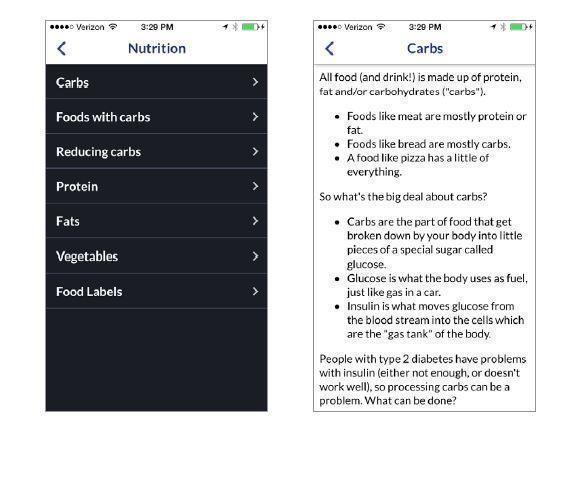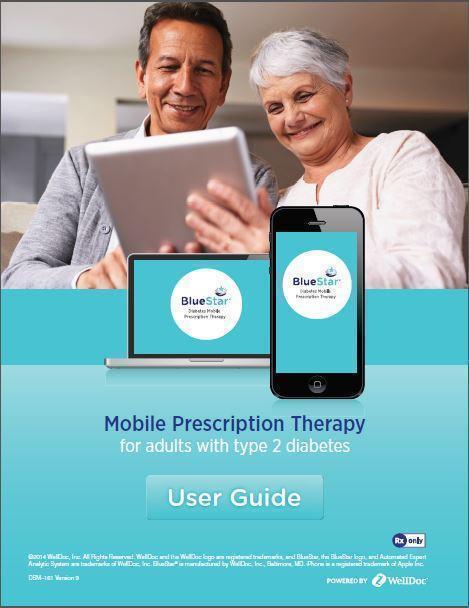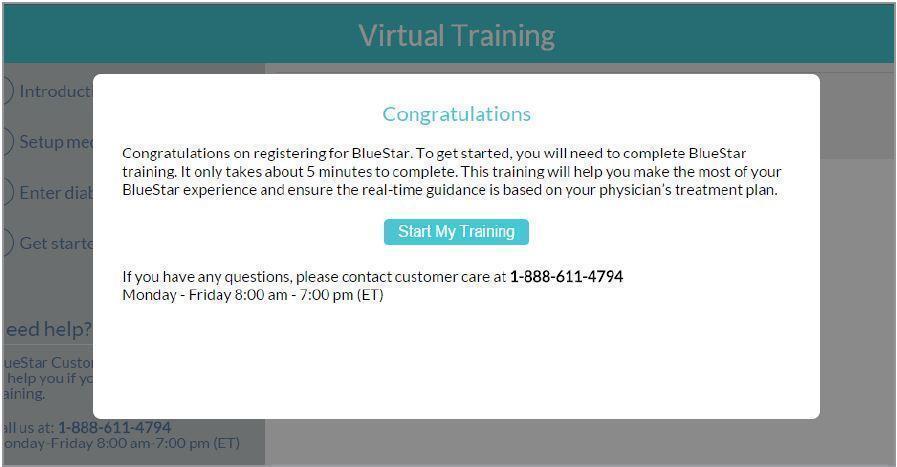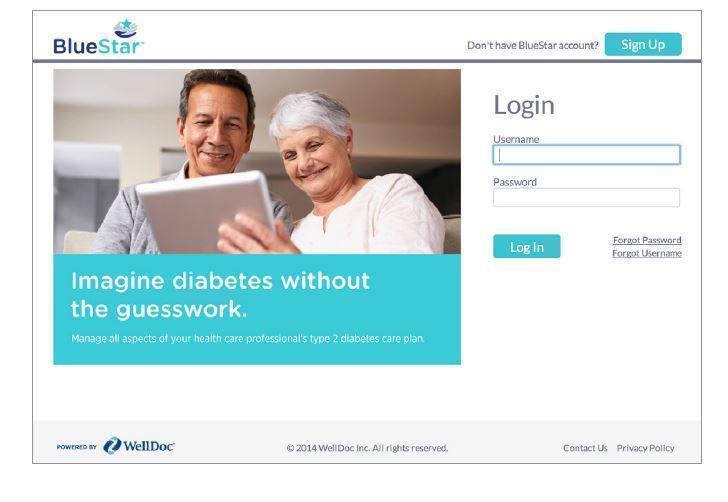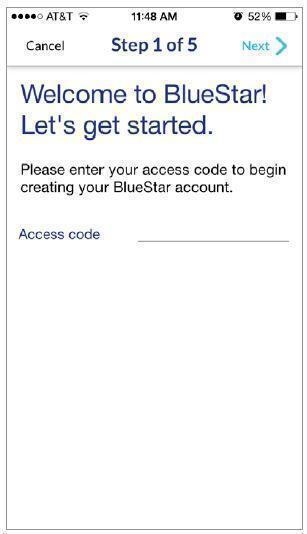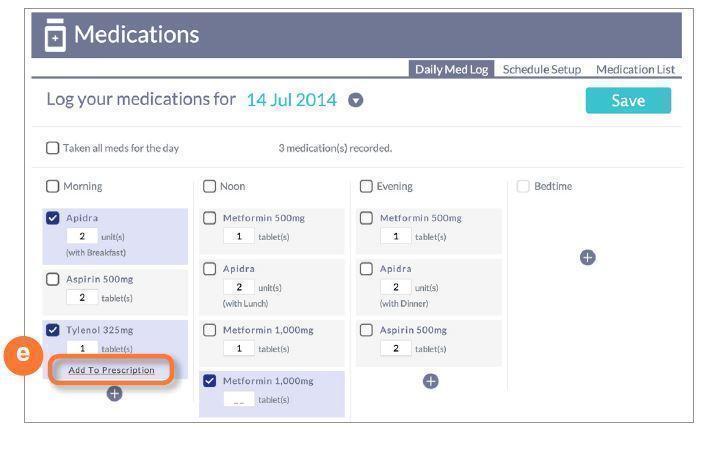 DRUG LABEL: WellDoc BlueStar
NDC: 89129-100
Manufacturer: WellDoc, Inc
Category: other | Type: MEDICAL DEVICE
Date: 20141014

Prescription Medical Device

Product Description

Introducing BlueStar
A new way to better manage your diabetes
BlueStar is the first mobile prescription therapy for adults with Type 2 diabetes. BlueStar gives you real-time guidance that makes managing diabetes between office visits easier and more doable. BlueStar must be prescribed by a provider.

Is BlueStar right for you?
Most people struggle to manage type 2 diabetes. Sometimes it is overwhelming and confusing. Understanding and remembering your doctor’s advice about medications, diet, and exercise isn’t easy. If you need help controlling your blood glucose, understanding everyday diabetes decisions, and keeping all your information in one place between office visits, BlueStar can help.

Diabetes Support, Anytime Anywhere™
BlueStar is not a pill or a shot — it is a completely new kind of approach to support you and help you manage your type 2 diabetes. BlueStar’s real-time feedback and guidance fits into your daily life to help you stay on track with your diabetes care plan. It works with you, struggles with you, achieves with you, and celebrates with you. BlueStar can help make living with diabetes easier which makes for a healthier, happier you.

BlueStar is accessible from your mobile phone or computer. It supports your healthcare provider’s instructions while helping you build your knowledge about diabetes and stay motivated.

Share your results with your doctor between visits
Before your next diabetes check-up, you can use BlueStar to send the information you put into BlueStar to your doctor. This can help your healthcare provider understand the challenges that you face between appointments. That way, during your office visit, you can both be ready to discuss your treatment plan and experiences managing diabetes.

Indication for use
BlueStar is indicated for use by healthcare providers and their adult patients, aged 21 years and older, who have type 2 diabetes. BlueStar is not intended to replace the care provided by a licensed healthcare professional, including prescriptions, diagnosis, or treatment. BlueStar is not indicated for people with type 1 diabetes, gestational diabetes or who use an insulin pump.

Important Safety Information: For medical questions, please contact your healthcare provider. If you are experiencing an emergency, please dial 911.

For more information visit www.bluestardiabetes.com or call BlueStar Customer Care at 1-888-611-4794

©2014 WellDoc, Inc. All Rights Reserved. WellDoc and the WellDoc logo are registered trademarks, and BlueStar, the BlueStar logo, and Automated Expert Analytic System are trademarks of WellDoc, Inc. BlueStar® is manufactured by WellDoc, Inc., Baltimore, MD. iPhone is a registered trademark of Apple Inc.

DSM-161 Version 09

BlueStar Customer Care

Ready to Answer Your Questions

BlueStar® Customer Care will be happy to help you with the following:
• How to use BlueStar
• Reporting errors when trying to use BlueStar
• Technical questions related to BlueStar on mobile and/or Web
• Questions about your prescription or health insurance reimbursement

Available: Monday-Friday, 8:00 a.m.-7:00 p.m. (ET)
Phone: (888) 611-4794

Getting Started

If you are new to BlueStar®, tap Sign Up to start registering or Log In with your username and password.

Virtual Training

• After you complete registration, you will be taken to BlueStar training video to learn how to set up your medication profile and enter
your diabetes data.

• Once you complete your training, it is important that you enter your medications in BlueStar so you can receive personalized guidance in managing your diabetes.

• The training video is available in BlueStar Help section for you to watch again if needed. To learn more about the Health Info Section, sending your SMART Visit report to your doctor before your visit or any other features within BlueStar, visit the Help section.

Getting Started (continued)

Follow the simple instructions below to create your BlueStar account.

To sign up:
a. Enter your Access Code
b. Enter your personal information
c. Tap on phone or click on website to agree to Terms of Service
d. Read Patient Authorization then tap or click on Accept
e. Tap or click on Create Account

Using BlueStar on Your Phone

BlueStar® is recommended for use on smartphones with an iOS 7 or greater or Android OS 4.0 or greater.

©2014 WellDoc, Inc. All Rights Reserved. WellDoc and the WellDoc logo are registered trademarks, and BlueStar, the BlueStar logo, and Automated Expert Analytic System are trademarks of WellDoc, Inc. BlueStar® is manufactured by WellDoc, Inc., Baltimore, MD. iPhone is a registered trademark of Apple Inc.

BlueStar Mobile

BlueStar® is the first prescription app for adults with Type 2 diabetes. BlueStar gives you real-time guidance that makes managing diabetes between office visits easier and more doable. BlueStar must be prescribed by a provider.

Log In

Enter your Username and Password then tap LOG IN

Trouble logging in?

Tap FORGOT PASSWORD? to retrieve your BlueStar password or FORGOT USERNAME? to retrieve your username

The next time you log in to BlueStar, you will be asked to create a 4-digit PIN.
Your PIN will make logging in faster and easier.
Enter your PIN on the dotted line each time you log in

Home Screen (mobile)

The BlueStar® carousel displays important information to help you manage your diabetes.

a. When BlueStar sees something interesting about your BG, a message is delivered to your carousel and logbook for that day.

b. Check for renewal reminders for your BlueStar prescription on the carousel

c. Get a daily boost with a new message to motivate you every day about your general health and well-being.

d. Short, 2- to 5-minute educational videos are designed to build your knowledge about diabetes and fit into your busy schedule. Each video is
available for 48 hours before it is replaced by the next one in the carousel.

e. Menu icon top left. Select the page you want to use or view.

f. Tap + icon top right from any screen to make a new entry

Making entries

Entering your blood glucose when you test and the medications you take can help you stay on track with your diabetes treatment plan. In return,
BlueStar gives you real-time guidance. Your experience is personalized so you understand more about your diabetes every day.

You can enter BG, carbs, exercise information, medications, and notes about your activities or how you are feeling each day. Below is the type of information you can input in BlueStar:

•Blood Glucose (BG)—enter your numbers every time your test your BG
• Carbs—enter how many carbs you had in a meal.
• Date/Time—displays current Date and Time. You have the flexibility to adjust the date to view or edit entries from an earlier date
• Activity Type—(Before Breakfast, Before Lunch, etc.) Your activity type defaults to how your Daily Schedule is preset on the website. You can update your Daily Schedule activity times in Settings
• Record Medications—record all your prescribed, over-the-counter medications, vitamins, and supplements. BlueStar will personalize your guidance based on your diabetes medications
• Add a Note—add important information that relates to your BG entry

Making entries (continued)

To make a New Entry
a. Tap on NEW ENTRY + ICON top right from any screen
b. Select DATE AND TIME.
Note: Will default to current date and time
c. Select ACTIVITY (Before Breakfast, Fasting, Before Lunch, etc.)
Note: Will default to an activity based on your Daily Schedule
d. Enter your Blood Glucose reading (BG) and Carbs (if applicable)

Medications (Medication list)

This is where you can view your medication information. It is important to record all meds you are taking—prescription, over-the-counter, supplements, and vitamins. BlueStar will give you personalized feedback based on your diabetes medications.

• Your Medication List gives you a view of your medications and how many times you take them daily.

Note: Always continue to take your medications as prescribed and confirm your prescription information with your healthcare provider at your earliest convenience.

Add Medication:

a. Tap the + button and enter at least 3 letters to search for a med
b. Select the medication you want to add
c. Enter how often you take your med
d. Enter the amount you take and save

Medications (Medication List) (continued)

Edit Medication:
You can change your dose, how often you take your med, or delete it from your list
a. Tap the PENCIL icon next to the medication name
b. Change how often you take your med or the amount you take
c. Tap the DELETE button to remove the med from your list

Medications (Schedule Setup and Med Reminders)

Here is where you can change your medication schedule and set a reminder to take your med.

Medication Schedule
Your medications are scheduled by Time of the Day (Morning, Noon, Evening and Bedtime or by Meal (Breakfast, Lunch or Dinner).\

Change your med schedule:
a. Tap the “arrow symbol”
b. Select another Meal or Time of the Day to take your med and save. Your med schedule is now updated for you to record in your Daily Med Log

Medication Reminders
You can set a reminder to take your medication.

To set a reminder:
a. Tap the slider next to “Reminder”
b. Tap the time to change if needed
A notification will pop up on your phone when it is time for you to take your med

Medications (Daily Med Log)

Your medications are displayed for a day according to your schedule (Meal or Time of the Day)

You can change the date if you want to record medications for an earlier day

a. Tap the Date
b. Change the day to a previous day

Tap to check you have taken all your meds for the day, by meal or time of day. You can also Tap one medication at a time.

a. Tap the Menu button
b. Select medications and then Daily Med Log
c. Tap to check that the meds you have taken

Medications (Daily Med Log) (continued)

You have the flexibility to add a dose of a med from your list or record a one-time dose of a med that is not on your list.

To add a dose of a new med:
a. Tap + to add med
b. Search for the med
c. Enter the amount you have taken
d. Tap DONE
e. Tap ADD TO PRESCRIPTION to add the med to your list

Real-Time Guidance

BlueStar supports you with instant guidance about any of your BGs that are entered in real time. BlueStar considers any BG that is entered within 2 hours of actually checking it to be a “real time” BG.

These messages can help you with:
• Immediate guidance on your BG value and how to correct it
• Information on nutrition
• Education about diabetes related health issues like blood pressure and cholesterol
• Messages to motivate and inspire you, including personal stories from other people with diabetes

Messages

BlueStar will send you personal messages through the message center. These messages can cover a range of topics, from introducing new features in BlueStar to reminding you to share your health info with your doctor before your next office visit. It is an easy way to communicate to you without cluttering your personal email.

a. The number displayed over the MESSAGES ICON shows you how many unread messages are in your Inbox. To view your messages, tap the MESSAGES NUMBER ICON
b. Tap the message you wish to view. Tap BACK ARROW to return to list of messages or DELETE to remove the message from your Inbox

Note: Your BlueStar® messaging system is a read-only system. You cannot send or forward messages from it.

Logbook

Logbook is a record of all your BG readings and related information such as carbs, meds, and notes you have entered into BlueStar®.
Be sure to check your BG targets set by your healthcare provider. You will see your targets listed right below dates and Activity Type.

To make a new Logbook entry:

a. Tap the + icon top right
b. Enter BLOOD GLUCOSE and CARBS for that meal
c. Select current DATE/TIME or an earlier date
d. Select ACTIVITY TYPE
e. Select ADD A NOTE to add important information about your BG entry

Tap graph icon right screen to see how your BG numbers are trending.

Note: Only the last thirty (30) days of data will appear in the logbook on your phone.

To edit any logbook entry, just click on it to make changes and then save them. If you would like to view your complete logbook display or print it, please Log In to the BlueStar website.

Logbook is where you can record and view your individual entries.

Health Info

You need to be connected to the Internet to access Health Info and to add new entries to it.
Health Info is where you can review your Medical History, Clinical Results, Preventive Health, Lifestyle, Provider, and Prescription information.

a. Tap on HEALTH INFO
b. Enter your PIN. If you have not created a PIN, BlueStar® will prompt you to create one
c. Tap your selection from the HEALTH INFO menu

IMPORTANT SAFETY INFORMATION:
For medical questions, please contact your healthcare provider. If you are experiencing an emergency, please dial 911.

Health Info (Medical History)

To complete your Medical History:a. Select year diagnosed with Diabetes
b. Tap Yes or No to answer each of the medical history questions
Note: If you’re not sure of the answer to some of the questions, be sure to discuss it with your healthcare provider.
Be sure to update your Medical History if there are changes to any diseases or conditions you may have.

IMPORTANT SAFETY INFORMATION:
For medical questions, please contact your healthcare provider. If you are experiencing an emergency, please dial 911.

Health Info (Clinical Results)

BlueStar lets you know if your numbers are in range, out of range, or you are overdue for a lab test.

To enter Clinical Results:a. Enter the numbers and dates for your current lab results and blood pressure check.

Remember to update your information each time you have new results.
If you’re not sure of the answers to some questions, be sure to discuss these with your healthcare provider.

IMPORTANT SAFETY INFORMATION:
For medical questions, please contact your healthcare provider. If you are experiencing an emergency, please dial 911.

Health Info (Preventive Health)

Preventive Health is a great tool for staying on track with exams and vaccinations that can help you manage your health. It lets you know if you are overdue or missing an item on the list.

a. Choose the date for each exam or vaccination you have had on the list

Remember to update your list whenever you have had a new exam or vaccination.

Health Info (Lifestyle)

Lifestyle displays your weight, height, calculates your BMI, and your smoking history.

a. Enter your current weight and choose date

b. Enter height in feet and inches and choose date

c. Your BMI is calculated automatically from your weight and height

d. Tap to enter your smoking history

Health Info (Provider)

You can review your healthcare provider information here and send a SMART Visit to your provider. To make changes to your healthcare provider information, you must call BlueStar® Customer Care at (888) 611-4794. Available: Monday-Friday, 8:00 a.m.-7:00 p.m. (ET).

What is a SMART Visit?
SMART Visit is a summary of the information you entered into BlueStar you can send to your healthcare provider. It includes your BGs, lab results, screening tests dates, vaccinations, and medications.

Send SMART Visit 2-3 days prior to an appointment so your provider will have the information to review with you during the visit.

a. Tap the Smart Visit button to send your information to your provider.

Health Info (Prescription Information)

Prescription Information lets you know when your BlueStar prescription will expire along with helpful information about refills.

Tips

Tips can help you build your knowledge and get useful tips about your health, nutrition, exercise, and BG.

Tap your selection from the TIPS menu. Most of the menu categories also have sub-menu topics to select from.

Help

HELP is here to help you make the most of BlueStar to stay on track with your diabetes care plan.
If you are new to BlueStar, Tour or Overview are great places to start.

• Virtual training—learn to setup your medication profile and enter diabetes data
• Welcome video—from the founder of BlueStar
• Overview—explains each main section of BlueStar
• Tour—takes you on a tour of how BlueStar works
• New Entry—explains what each entry category is for
• About BlueStar—tells you what version you are using of the mobile app
• Privacy Policy
• Tap the Customer Care number to speak with a BlueStar customer care representative. Available: Monday-Friday, 8:00 a.m.-7:00 p.m. (ET).

Settings

Use PIN Settings to create or change your PIN number or lock BlueStar®.
You will need to use a PIN to access your Health Info.

To create or change your PIN:

a. Tap on the COG icon
b. Tap on CREATE PIN or CHANGE PIN
c. Enter your current PIN on dotted line
d. Enter new PIN on dotted line then re-enter

To lock BlueStar:
a. Move the LOCK BLUESTAR slider control to the right to lock your application

Using BlueStar on the Web

BlueStar® is recommended for use on the following web browsers:
Internet Explorer 10 and 11
Mozilla Firefox 31 and 32,
Google Chrome 37
Safari 7.0.6

BlueStar® is recommended for use on the following tablets:
iPad Retina/Air - 2048x1536
iPad Mini - 1024x768
Samsung tab 10.1 - 1280x800
Samsung tab 7.0 - 1024x600

Log In

BlueStar® is the first prescription app for adults with Type 2 diabetes. BlueStar gives you real-time guidance that makes managing diabetes between office visits easier and more doable. BlueStar must be prescribed by a provider.

Log In
Enter your Username and Password then click LOG IN

Trouble logging in?
Click FORGOT PASSWORD? to retrieve your BlueStar password or FORGOT USERNAME? to retrieve your username

Home Screen

The BlueStar® home screen carousel displays important information to help you manage your diabetes and build your knowledge.

The carousel on the BlueStar home screen displays your last 4 BG entries. When BlueStar sees something interesting about your BG, a message is delivered to your carousel and logbook for that day.

Get a daily boost with a new message to motivate you each day about your general health and well-being.

Short, 2- to 5-minute educational videos are designed to build your knowledge about diabetes and fit into your busy schedule. Each video is available for 48 hours before it is replaced by a new one.

Home Screen (continued)

Check for renewal reminders for your BlueStar prescription on the carousel.

a. Health-related tips and reminders for completing your Profile

b. Profile status shows how much of your Health Info Profile is complete and what sections may need completing. Click on the pencil icon to complete any section. Or click on HEALTH INFO from the main menu to complete your profile.
Keeping your Clinical Results, Preventive Health, Medical History, and Lifestyle information up to date will help us customize BlueStar™ for you.

c. SMART Visit is a summary of the information you entered into BlueStar you can send to your healthcare provider. It includes your BGs, lab results, screening tests dates, vaccinations, and medications.
Send SMART Visit 2-3 days prior to an appointment so your provider will have the information to review with you during the visit. Click on the SMART VISIT button to send your information.

Making Entries

Entering your blood glucose and medications can help you stay on track with your diabetes treatment plan. That way BlueStar can personalize real-time guidance for you every day.

You can enter information for any of the following categories:
• Blood Glucose (BG): enter your numbers after you test yourself
• Carbs: enter how many carbs you had in a meal
• Date/Time: displays current Date and Time. You have the flexibility to adjust the date/time to enter entries from an earlier date
• Activity Type: (Before Breakfast, Fasting, Before Lunch, etc.) This defaults to how your Daily Schedule is preset. You can update your Daily Schedule activity times in Settings
• Record Medications: record all your prescribed, over-the-counter medications, vitamins, and supplements. BlueStar will personalize your guidance based on your diabetes medications
• Add a Note: add important information that relates to your BG entry

To make a New Entry:
a. Click on New Entry + icon top right from any screen
b. Select DATE AND TIME. Note: Will default to current date and time
c. Select ACTIVITY (Breakfast, Fasting, Before Lunch, etc.) Note: Will default to an activity based on your Daily Schedule
d. Enter your BLOOD GLUCOSE reading (BG) and CARBS (if applicable)
e. Click on TAKEN ALL MEDS FOR THE DAY or individual medications you took for that meal or time of the day
f. Click on ADD A NOTE to add information about your BG entry
g. Click on SAVE to save your entry information

Medications (Medication List)

This is where you can view your medication information. It is important to record all meds you are taking—prescription, over-the-counter, supplements, and vitamins. BlueStar will personalize your guidance, based on your diabetes medications.

• Your Medication List gives you a view of your medications and how many times you take them daily. You can add a new med to your list, make changes to a med, or delete a med from your list

Note: Always continue to take your medications as prescribed and confirm your prescription information with your healthcare provider at your earliest convenience.

Add a new medication:
a. Enter at least 3 letters to search for a med
b. Select the medication you want to add
c. Enter how often you take your med
d. Enter the amount you take and save

Edit medication:
You can change the strength of your med, your dose, how often you take your med, or delete it from your list
a. Click pencil icon next to the medication name
b. Change the arrow by the med name to change the strength
c. Click the arrow to change the reason you take your med, how often you take it, or the amount you take
d. Click the delete button to remove the med from you list
e. Click save

Medications (Schedule Setup)

Your medications are scheduled by Time of the Day (Morning, Noon, Evening and Bedtime or by Meal (Breakfast, Lunch or Dinner)

Change your med schedule:
a. Change your schedule by dragging your med to another time of day or meal type. Your med schedule is now updated for you to record in your Daily Med Log

Medication reminders:
a. You can set a reminder to take your medication. Click on the bell icon by the meal type or time of day. Select the reminder time and save. A notification will pop up on your phone when it is time for you to take your med

Medications (Daily Med Log)

Your medications are displayed for a day according to your schedule (Meal or Time of Day)

You can change the date if you want to record medications for an earlier day
a. Select the arrow by the date
b Use to calendar to change the day to a previous day

Check that you have taken all your meds for the day, by meal or time of day. You can also record one medication at a time.
a. Click Medications
b. Daily Med Log
c. Check the medications you have taken

You have the flexibility to add a dose of med from your list or record a one-time dose of a med that is not on your med list

Medications (Daily Med Log) (continued)

Add a dose of med from your list:
a. Click + in the meal or time of day
b. Select a med from your list
c. Click to check that you have taken your med

Medications (Daily Med Log) (continued)

To add a one-time dose of a new med:
a. Search for the med
b. Select to add med
c. Enter the amount you have taken
d. Click OK
e. Click add to prescription to add the med to your list

Real-Time Guidance

BlueStar supports you with instant guidance about any of your BGs that are entered in real time. BlueStar considers any BG that is entered
within 2 hours of actually checking it to be a “real time” BG.

These messages can help you with:
• Immediate guidance on your BG value and how to correct it
• Information on nutrition
• Education about diabetes related health issues like blood pressure and cholesterol
• Messages to motivate and inspire you, including personal stories from other people with diabetes

Messages

BlueStar will send you personal messages through the message center. These messages can cover a range of topics, from introducing new features in BlueStar to reminding you to share your health info with your doctor before your next office visit. It is an easy way to communicate to you without cluttering your personal email.

To view your messages:
a. Click on MESSAGES at the top of the screen
b. Review your list of messages and click on the message you would like to read
c. Click X icon to delete a message
Note: Your BlueStar™ messaging system is a read-only system. You cannot send or forward messages from it

Logbook

Logbook is a record of all your BG readings and related information such as carbs, meds, and notes you have entered into BlueStar. You can view and edit your entries here.

Be sure to check your BG targets set by your healthcare provider. You will see your targets listed right below dates and Activity Type.

To view your entries:

a. Click on date ranges to set the date range you want to view
b. Click on Activity Type to change the view to view by time

To make a new entry:
c. Click on any empty square on your Logbook to add an entry for that date and activity type or click on the + icon top right screen

To edit Logbook entries:
d. Click on any entry to make changes, including entries for earlier dates

To view Trending Graph:
e. Click Graph top right screen to see how your BG numbers are trending

Health Info (Medical History)

Use Health Info to record your important health information for BlueStar®, including:
• Medical History (other medical problems that can affect your diabetes management)
• Clinical Results (A1C, cholesterol, kidney function tests, etc.).
• Preventive Health (vaccinations, foot exam, eye exam, etc.).
• Lifestyle (height, weight, smoking history).
• Provider
• Prescription

IMPORTANT SAFETY INFORMATION:
For medical questions, please contact your healthcare provider. If you are experiencing an emergency, please dial 911.

a. Click any of these links to learn more about these diseases and conditions

To complete your Medical History:
a. Select year diagnosed with Diabetes
b. Click Yes or No to answer each of the medical history questions
Note: If you’re not sure of the answer to some of the questions, be sure to discuss it with your healthcare provider.
Be sure to update your Medical History if there are changes to any diseases or conditions you may have.

Health Info (Clinical Results)

BlueStar lets you know if your numbers are in range, out of range, or you are overdue for a lab test

To enter Clinical Results:
a. Enter the numbers and dates for your current lab results and blood pressure check
Remember to update your information each time you have new results If you’re not sure of the answers to some questions, be sure to discuss these with your healthcare provider

IMPORTANT SAFETY INFORMATION:
For medical questions, please contact your healthcare provider. If you are experiencing an emergency, please dial 911.

Health Info (Preventive Health)

Preventive Health is a great tool for staying on track with exams and vaccinations that can help you manage your health. It lets you know if you are overdue for an exam or vaccination or missing an item on the list.

a. Choose the date for each exam or vaccination you have had on the list
Remember to update your list whenever you have had a new exam or vaccination

Health Info (Lifestyle)

Lifestyle displays your weight, height, calculates your BMI, and your smoking history.

a. Enter your current weight and choose date
b. Enter height in feet and inches and choose date
c. Your BMI is calculated automatically from your weight and height
d. Click Tobacco Usage to enter your smoking history

Health Info (Provider)

This is where you can review your healthcare provider information nd send a SMART Visit to your healthcare provider. To make changes to your healthcare provider information, you must call BlueStar® Customer Care at (888) 611-4794. Available: Monday-Friday, 8:00 a.m.-7:00 p.m. (ET).

What is a SMART Visit?
SMART Visit is a summary of the information you entered into BlueStar you can send to your healthcare provider. It includes your BGs, lab results, screening tests dates, vaccinations, and medications.

Send SMART Visit 2-3 days prior to an appointment so your provider will have the information to review with you during the visit.

a. Click the Smart Visit button to send your information to your provider.

Health Info (Prescription Information)

Prescription Information lets you know when your BlueStar prescription will expire along with helpful information about refills.

Settings

Click on SETTINGS top right on any screen to make updates to any of your settings. Then select the tab for the screen you would like to update.

• My Profile: your email address
Note: No changes can be made after registration to basic profile information. If you have changed your name due to marriage, divorce or other legal means, please call Customer Care at (888) 611-4794. Available: Monday-Friday, 8:00 a.m.-7:00 p.m. (ET).

• Security and Password: Password, Security Questions, Username

• Daily Schedule: Breakfast, Lunch, Dinner, Bedtime Schedules

• Notifications: Lets BlueStar know which notifications you would like to receive

Help

HELP is where you can:
• Watch Virtual Training and BlueStar Welcome Video
• Download a PDF version of BlueStar User Guide
• Send a link to your phone to download BlueStar Diabetes Mobile app
• Get contact information to speak to a Customer Care representative

BlueStar Diabetes Mobile Prescription Therapy

INDICATION FOR USE
BlueStar™ is indicated for use by healthcare providers and their adult patients, aged 21 years and older, who have type 2 diabetes. BlueStar is not intended to replace the care provided by a licensed healthcare professional, including prescriptions, diagnosis, or treatment. BlueStar is not indicated for people with type 1 diabetes, gestational diabetes or who use an insulin pump.

PRODUCT DESCRIPTION
BlueStar is a mobile prescription therapy for adults with type 2 diabetes. BlueStar gives people living with type 2 diabetes real-time guidance to help improve the self-management of their diabetes. BlueStar also gives healthcare providers clinical decision support to help optimize patients’ treatment regimens. BlueStar must be prescribed by a licensed healthcare provider.

CAUTION
Federal law restricts this device to sale, distribution and use by or on the order of any licensed healthcare provider. BlueStar is for Single Patient Use Only. Allowing other people to enter their self-management data into your BlueStar could impact the ability for your physician to accurately assess and manage your diabetes. Before using BlueStar please read all instructions on incorporating your physician’s treatment plan and entering your diabetes self-management data into BlueStar. Certified BlueStar Trainers are available to help you begin using BlueStar; to speak with a trainer call 1-888-611-4794. If you experience a medical emergency while using BlueStar, please contact emergency services (dial 911).

DOSAGE AND ADMINISTRATION
The National Council for Prescription Drug Programs (NCPDP) has determined the Pack Size for BlueStar: 1 Each = 30 days.

GETTING STARTED
If your physician has prescribed BlueStar or provided you with a sample, visit www.bluestardiabetes.com to get started. Click PATIENT LOGIN. Then click, SIGN UP to start registering. Follow the instructions on the website to create your BlueStar account. You need an Access Code to finalize the account set-up. The Access Code will either be provided by your physician or BlueStar Customer Care. BlueStar is dispensed by a licensed pharmacist. You will need to speak with a pharmacist before accessing your BlueStar Prescription is filled.

ACCESSING BLUESTAR
BlueStar is available on smartphones, computers and tablets. On smartphones it is recommended for use on devices with an iOS 7 or greater or Android OS 4.0 or greater. On the web it is recommended for use on computers with Internet Explorer 10 and 11, Mozilla Firefox 29 and 30 and Chrome 35.

IMPORTANT SAFETY INFORMATION
For medical questions, please contact your healthcare provider. If you are experiencing an emergency, please dial 911. For complete instructions on how to use BlueStar, please refer the user guide available on the BlueStar web application under HELP. For more information visit www.bluestardiabetes.com or call BlueStar Customer Care at 1-888-611-4794.

OUR COMMITMENT TO YOU
Our goal is to provide you with quality health care products and dedicated customer service. If you are not fully satisfied with BlueStar, or if you have questions about the use of any WellDoc product, please call us at 1-888-611-4794.

ABOUT BLUESTAR
Powered by WellDoc, 1501 Saint Paul Street, Suite 118, Baltimore, MD. 21202. BlueStar (product) Version 2.3 released on 10/09/2014

BlueStar User Guide, DSM-161 Version 9 published on BlueStar web application on 10/09/2014

©2014 WellDoc, Inc. All Rights Reserved. WellDoc and the WellDoc logo are registered trademarks, and BlueStar, the BlueStar logo, and Automated Expert Analytic System are trademarks of WellDoc, Inc. BlueStar™ is manufactured by WellDoc, Inc., Baltimore, MD. iPhone is a registered trademark of Apple Inc.

Access to complete User Guide can be found under the HELP section on the web site at:
www.bluestardiabetes.com/Portal/Guest/Login.htm.
COM-002-0072